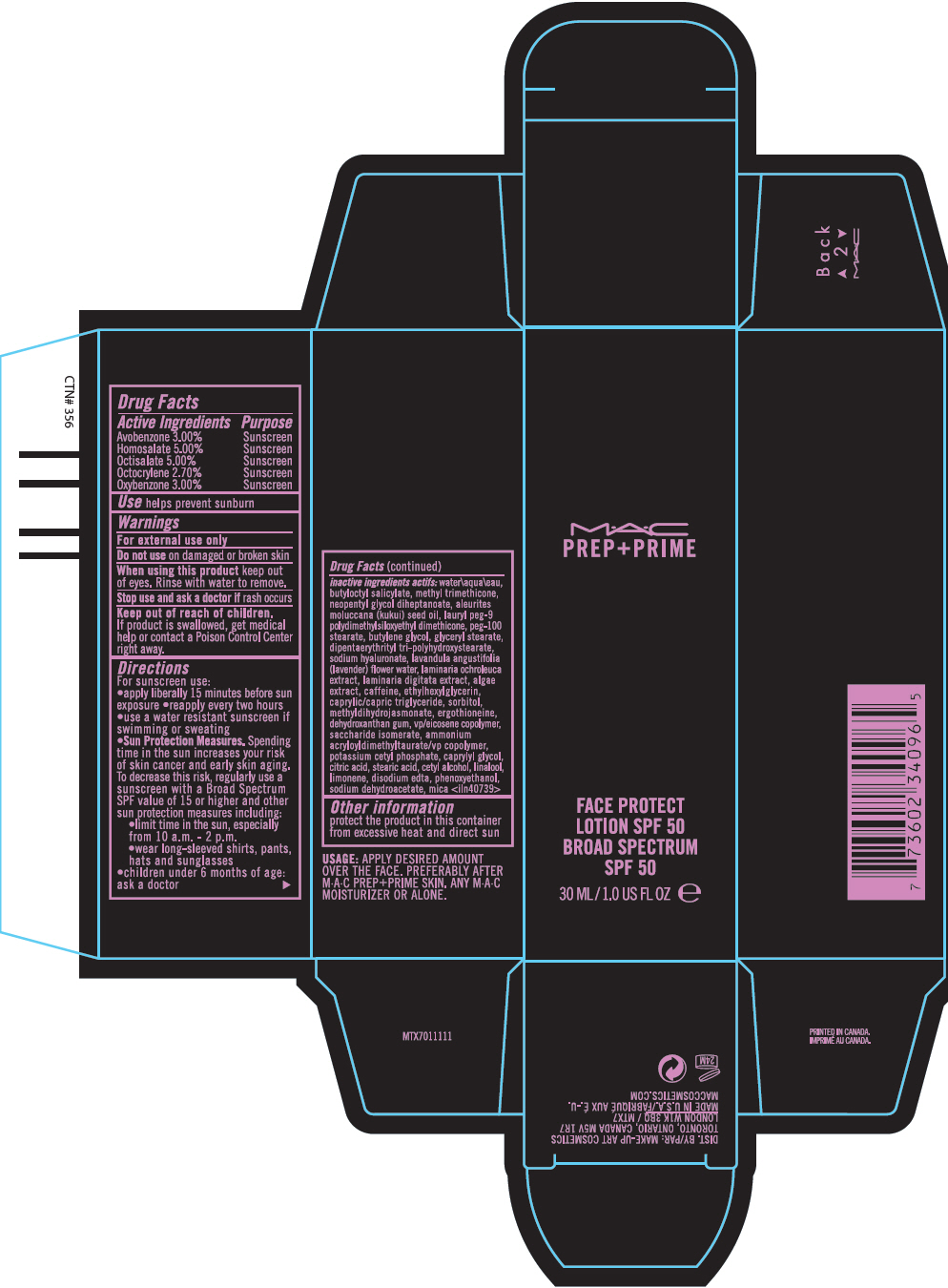 DRUG LABEL: MAC PREP AND PRIME FACE PROTECT BROAD SPECTRUM SPF 50
NDC: 40046-0063 | Form: LOTION
Manufacturer: MAKEUP ART COSMETICS
Category: otc | Type: HUMAN OTC DRUG LABEL
Date: 20241225

ACTIVE INGREDIENTS: AVOBENZONE 30 mg/1 mL; HOMOSALATE 50 mg/1 mL; OCTISALATE 50 mg/1 mL; OCTOCRYLENE 27 mg/1 mL; OXYBENZONE 30 mg/1 mL
INACTIVE INGREDIENTS: WATER; BUTYLOCTYL SALICYLATE; METHYL TRIMETHICONE; NEOPENTYL GLYCOL DIHEPTANOATE; KUKUI NUT OIL; LAURYL PEG-9 POLYDIMETHYLSILOXYETHYL DIMETHICONE; PEG-100 STEARATE; BUTYLENE GLYCOL; GLYCERYL MONOSTEARATE; DIPENTAERYTHRITYL TRI-POLYHYDROXYSTEARATE; HYALURONATE SODIUM; CAFFEINE; ETHYLHEXYLGLYCERIN; MEDIUM-CHAIN TRIGLYCERIDES; SORBITOL; METHYL DIHYDROJASMONATE (SYNTHETIC); ERGOTHIONEINE; DEHYDROXANTHAN GUM; SACCHARIDE ISOMERATE; AMMONIUM ACRYLOYLDIMETHYLTAURATE/VP COPOLYMER; POTASSIUM CETYL PHOSPHATE; CAPRYLYL GLYCOL; CITRIC ACID MONOHYDRATE; STEARIC ACID; CETYL ALCOHOL; LINALOOL, (+/-)-; EDETATE DISODIUM ANHYDROUS; PHENOXYETHANOL; SODIUM DEHYDROACETATE; MICA

MAC PREP AND PRIME FACE PROTECT LOTION BROAD SPECTRUM SPF 50

Drug Facts

ACTIVE INGREDIENT

Active Ingredients | Purpose
Avobenzone 3.00% | Sunscreen
Homosalate 5.00% | Sunscreen
Octisalate 5.00% | Sunscreen
Octocrylene 2.70% | Sunscreen
Oxybenzone 3.00% | Sunscreen

Use

helps prevent sunburn

Warnings

For external use only

Do not use on damaged or broken skin

When using this product keep out of eyes. Rinse with water to remove.

Stop use and ask a doctor if rash occurs

Keep out of reach of children. If product is swallowed, get medical help or contact a Poison Control Center right away.

Directions

For sunscreen use:

- apply liberally 15 minutes before sun exposure
- reapply every two hours
- use a water resistant sunscreen if swimming or sweating
- Sun Protection Measures. Spending time in the sun increases your risk of skin cancer and early skin aging. To decrease this risk, regularly use a sunscreen with a Broad Spectrum SPF value of 15 or higher and other sun protection measures including:
  - limit time in the sun, especially from 10 a.m. - 2 p.m.
  - wear long-sleeved shirts, pants, hats and sunglasses
- children under 6 months of age: ask a doctor

inactive ingredients

water\aqua\eau, butyloctyl salicylate, methyl trimethicone, neopentyl glycol diheptanoate, aleurites moluccana (kukui) seed oil, lauryl peg-9 polydimethylsiloxyethyl dimethicone, peg-100 stearate, butylene glycol, glyceryl stearate, dipentaerythrityl tri-polyhydroxystearate, sodium hyaluronate, lavandula angustifolia (lavender) flower water, laminaria ochroleuca extract, laminaria digitata extract, algae extract, caffeine, ethylhexylglycerin, caprylic/capric triglyceride, sorbitol, methyldihydrojasmonate, ergothioneine, dehydroxanthan gum, vp/eicosene copolymer, saccharide isomerate, ammonium acryloyldimethyltaurate/vp copolymer, potassium cetyl phosphate, caprylyl glycol, citric acid, stearic acid, cetyl alcohol, linalool, limonene, disodium edta, phenoxyethanol, sodium dehydroacetate, mica <iln40739>

Other information

protect the product in this container from excessive heat and direct sun

DIST. BY: MAKE-UP ART COSMETICS
TORONTO, ONTARIO, CANADA M5V 1R7
LONDON W1K 3BQ / MTX7

PRINCIPAL DISPLAY PANEL - 30 ML Tube Carton

M•A•C
PREP+PRIME

FACE PROTECT
LOTION SPF 50
BROAD SPECTRUM
SPF 50

30 ML/1.0 US FL OZ e